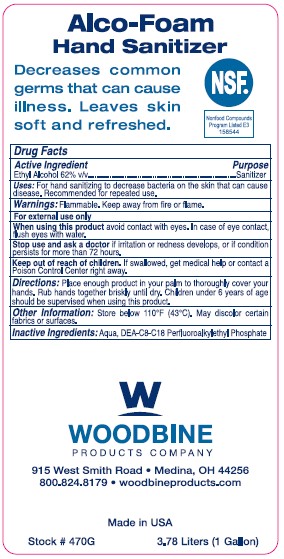 DRUG LABEL: FoamFresh Alco-Foam Hand Sanitizer
NDC: 11429-1004 | Form: LIQUID
Manufacturer: Woodbine Products Company
Category: otc | Type: HUMAN OTC DRUG LABEL
Date: 20251204

ACTIVE INGREDIENTS: ALCOHOL 62 mL/100 mL
INACTIVE INGREDIENTS: WATER; DIETHANOLAMINE BIS(C8-C18 PERFLUOROALKYLETHYL)PHOSPHATE

Drug Facts 11429-1004

Active Ingredient

Ethyl Alcohol 62% v/v

Purpose

Sanitizer

Uses:

For hand sanitizing to decrease bacteria on the skin that could cause disease.

Recommended for repeated use.

Warnings:

Flammable. Keep away from fire or flame

For external use only

When using this product avoid contact with eyes.

In case of eye contact, flush eyes with water.

Stop use and ask a doctor if irritation or redness develops, or if condition persists for more than 72 hours.

Keep out of reach of children.

If swallowed, get medical help or contact a Poison Control Center right away.

Directions:

Place enough product in your palm to thoroughly cover your hands.

Rub hands together briskly until dry.

Children under 6 years of age should be supervised when using this product.

Other information:

Store below 110 F (43 C).

May discolor certain fabrics or surfaces.

Inactive ingredients:

Aqua, DEA-C8-18 Perfluoroalkylethyl Phosphate

PACKAGE LABEL

Alco-Foam

Hand Sanitizer

Decreases common

germs thatcan cause

illness. Leaves skin

soft and refreshed.

NSF

Nonfood Compounds

Program Listed E3

158544

Woodbine Products Company

915 West Smith Road

Medina, Ohio 44256

www.woodbineproducts.com

Made in the USA

Stock # 470G 3.78 Liters (1 Gallon)